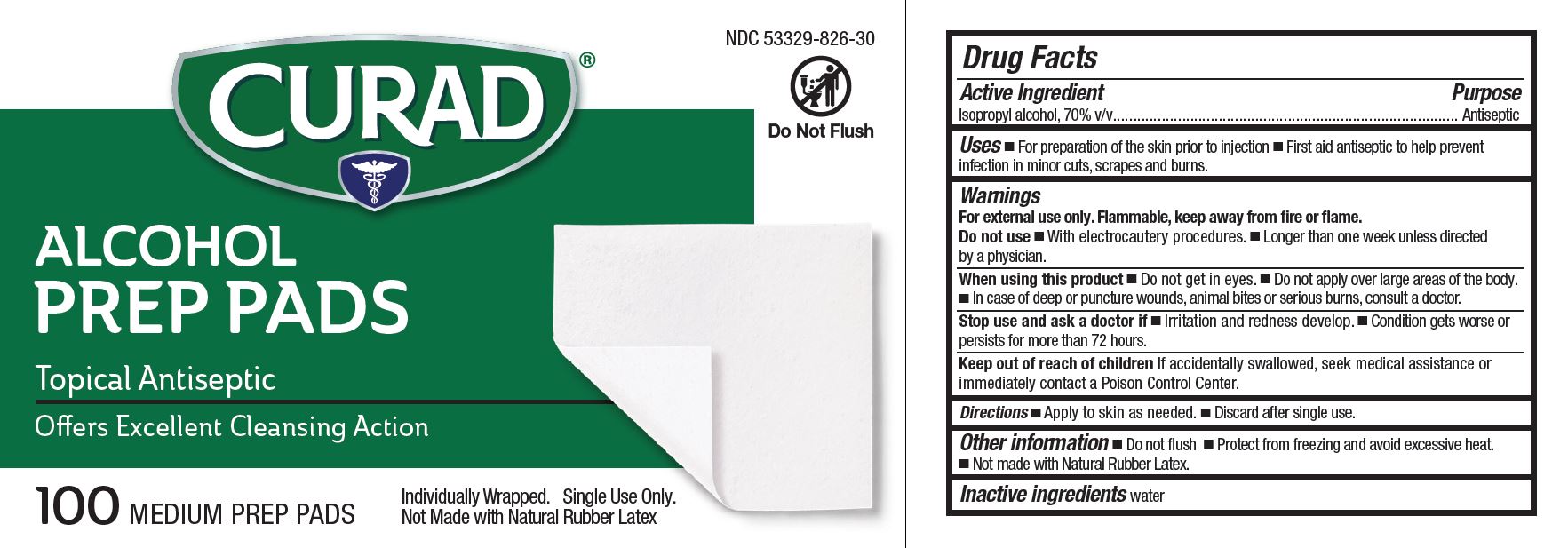 DRUG LABEL: Curad Alcohol
NDC: 53329-826 | Form: SWAB
Manufacturer: Medline Industries, LP
Category: otc | Type: HUMAN OTC DRUG LABEL
Date: 20241210

ACTIVE INGREDIENTS: ISOPROPYL ALCOHOL 70 mL/100 mL
INACTIVE INGREDIENTS: WATER

826 Curad Sterile Alcohol Prep Pads

Active ingredient

Isopropyl alcohol, 70% v/v

Purpose

Antiseptic

Uses

- For preparation of the skin prior to an injection
- First aid antiseptic to help prevent infection in minor cuts, scrapes and burns

Warnings

For external use only. Flammable, keep away from fire or flame.

Do not use

- with electrocautery procedures
- longer than 1 week unless directed by a physician

When using this product

- do not get into eyes
- do not apply over large areas of the body
- in case of deep or puncture wounds, animal bites or serious burns, consult a doctor

Stop use and ask a doctor if

- irritation and redness develop
- condition gets worse or persists for more than 72 hours

Keep out of reach of children.

If accidentally swallowed, get medical assistance or immediately contact a Poison Control Center.

Directions

- Apply to skin as needed.
- Discard after single use.

Other information

- Protect from freezing and avoid excessive heat.
- Not made with Natural Rubber Latex.

Inactive ingredients

water

Manufacturing Information

Manufactured for:
Medline Industries, LP
Three Lakes Drive, Northfield, IL 60093 USA
Made in USA with domestic and foreign materials
www.curad.com
1-800-633-5463
REF: CUR45585RB
V1 RE22LPD